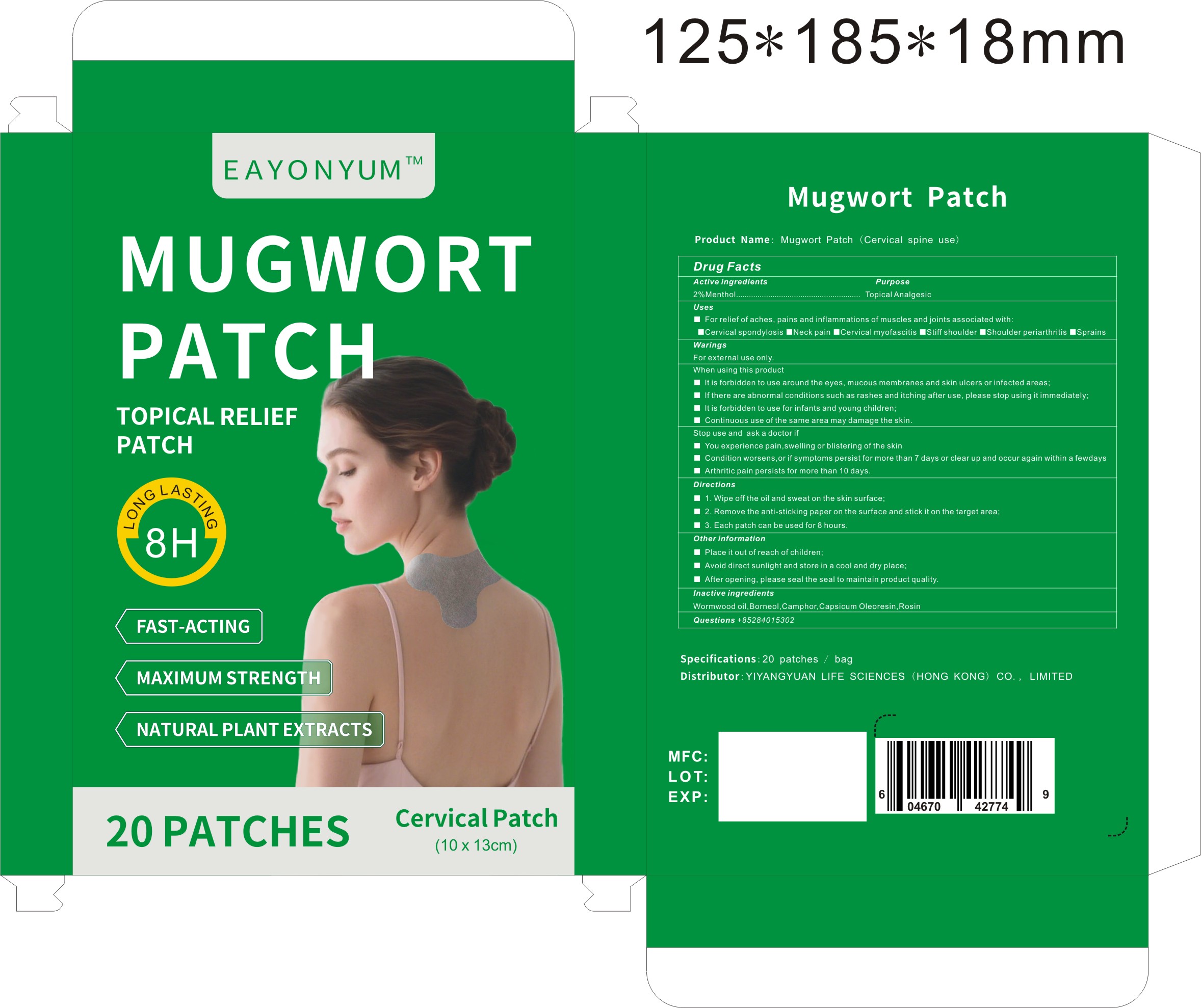 DRUG LABEL: Mugwort Patch (Cervical spine use)
NDC: 87267-002 | Form: PATCH
Manufacturer: YIYANGYUAN LIFE SCIENCES (HONG KONG) CO., LIMITED
Category: otc | Type: HUMAN OTC DRUG LABEL
Date: 20260104

ACTIVE INGREDIENTS: MENTHOL 2 g/100 g
INACTIVE INGREDIENTS: WORMWOOD OIL; ROSIN; CAMPHOR, (-)-; BORNEOL; CAPSICUM OLEORESIN

87267-002-Mugwort Patch (Cervical spine use)

PURPOSE

For relief of aches, pains and inflammations of muscles and joints associated with:Cervical spondylosis Neck pain Cervical myofascitis Stiff shoulder Shoulder periarthritis Sprains

Active ingredients
2%Menth01.........................
Purpose
Topical Analgesic

WARNINGS

WaringsFor external use only.

Place it out of reach of children;

When using this product
It is forbidden to use around the eyes,mucous membranes and skin ulcers or infected areas;
If there are abnormal conditions such as rashes and itching after use,please stop using it immediately;It is forbidden to use for infants and young children;
Continuous use of the same area may damage the skin.

Directions
1. Wipe off the oil and sweat on the skin surface;
2.Remove the anti-sticking paper on the surface and stick it on the target area;
3.Each patch can be used for 8 hours.

INACTIVE INGREDIENT

Inactive ingredientsWormwood oil,Borneol,Camphor,Capsicum Oleoresin,Rosin